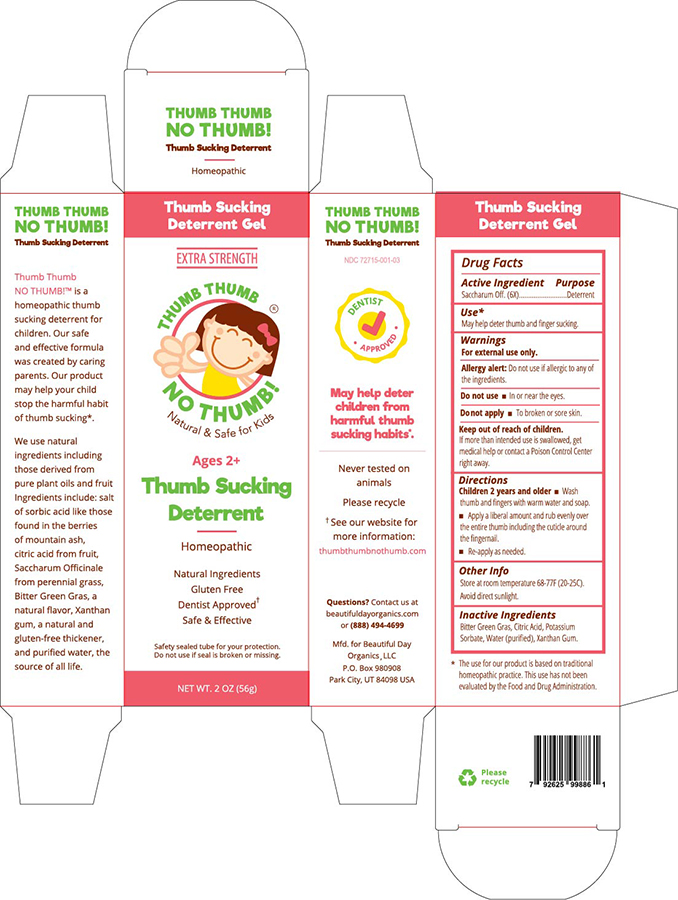 DRUG LABEL: Thumb Thumb No Thumb
NDC: 72715-001 | Form: GEL
Manufacturer: Beautiful Day Organics, LLC
Category: homeopathic | Type: HUMAN OTC DRUG LABEL
Date: 20230109

ACTIVE INGREDIENTS: SACCHARUM OFFICINARUM WHOLE 6 [hp_X]/58 g
INACTIVE INGREDIENTS: POTASSIUM SORBATE; WATER; CITRIC ACID MONOHYDRATE; XANTHAN GUM

Drug Facts

Active Ingredient
Saccharum Off. (6X)..........................

Purpose-Deterrent

INDICATIONS AND USAGE

Use-May help deter thumb and finger sucking.

Warnings:For external use only.
Allergy alert: Do not use if allergic to any of the ingredients

Do not use In or near the eyes.
Do not apply To broken or sore skin.

Keep out of reach of children.
If more than intended use is swallowed, get
medical help or contact a Poison Control Center
right away.

DOSAGE AND ADMINISTRATION

Directions: Children 2 years and older: Wash thumb and fingers with warm water and soap.
Apply a liberal amount and rub evenly over
the entire thumb including the cuticle around
the fingernail.
Re-apply as needed.

Inactive Ingredients: Bitter Green Gras, Citric Acid, Potassium
Sorbate, Water (purified), Xanthan Gum.

OTHER SAFETY INFORMATION

Other Info: Store at room temperature 68-77F (20-25C).Avoid direct sunlight.

PACKAGE LABEL

Thumb Thumb No Thumb NDC 72715-001-03

NET WT 2.0 OZ (56g)